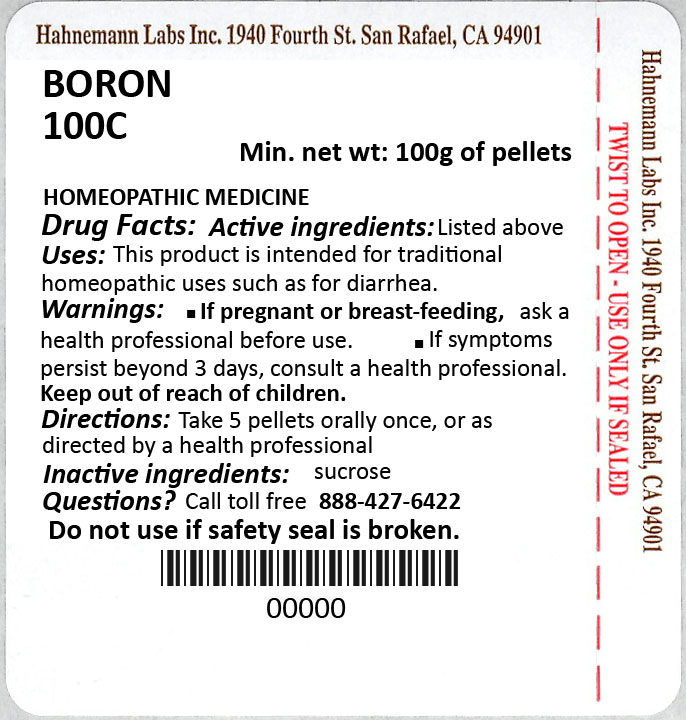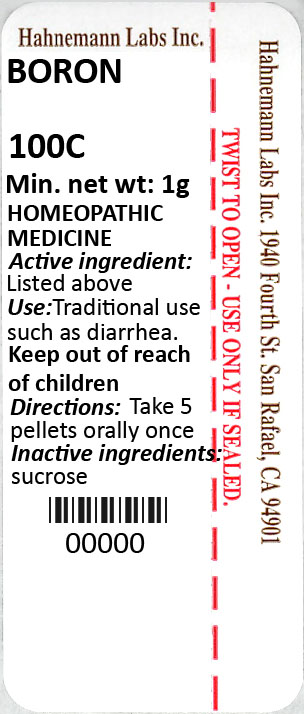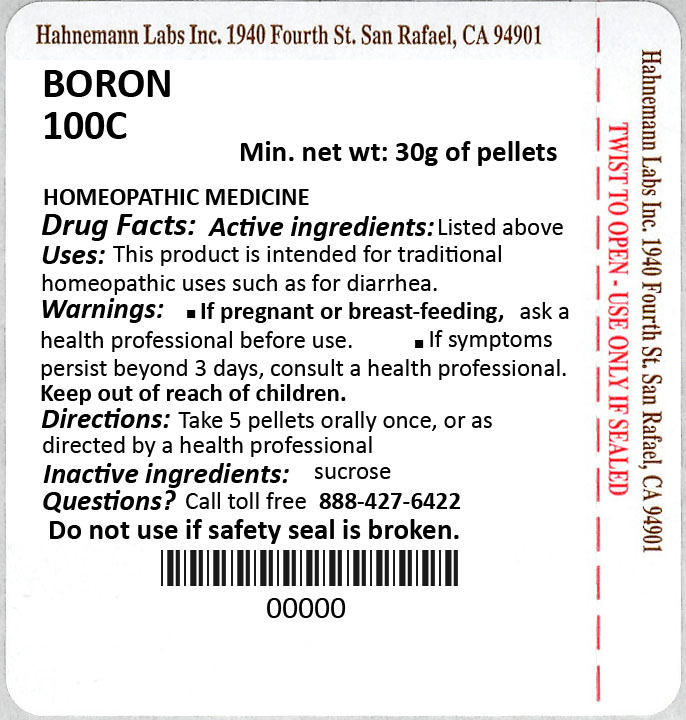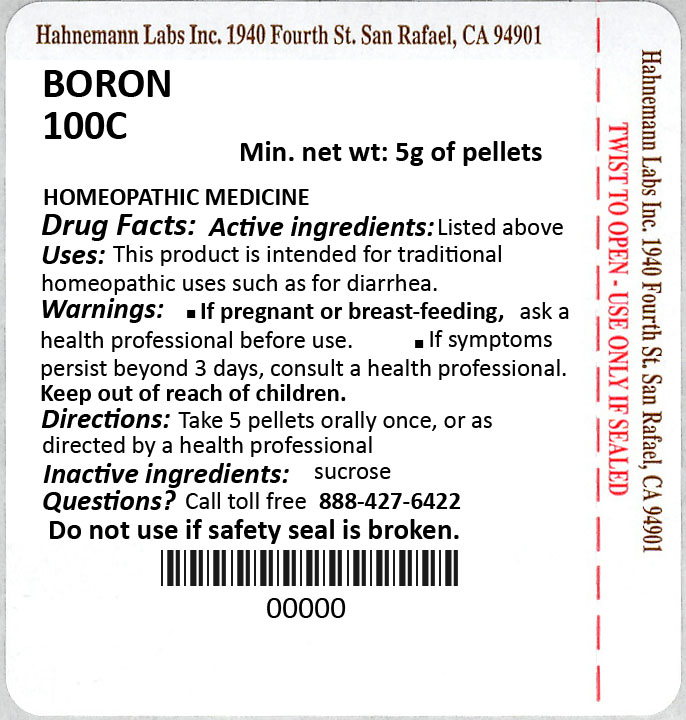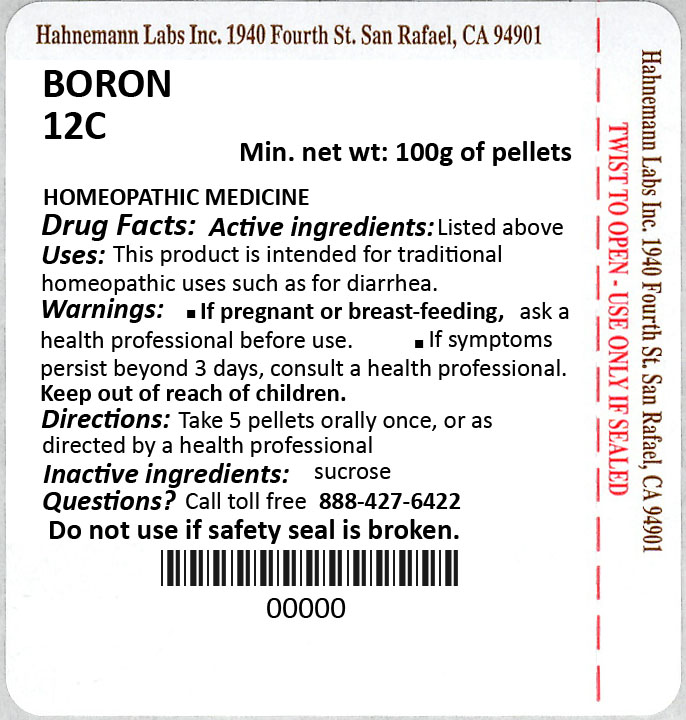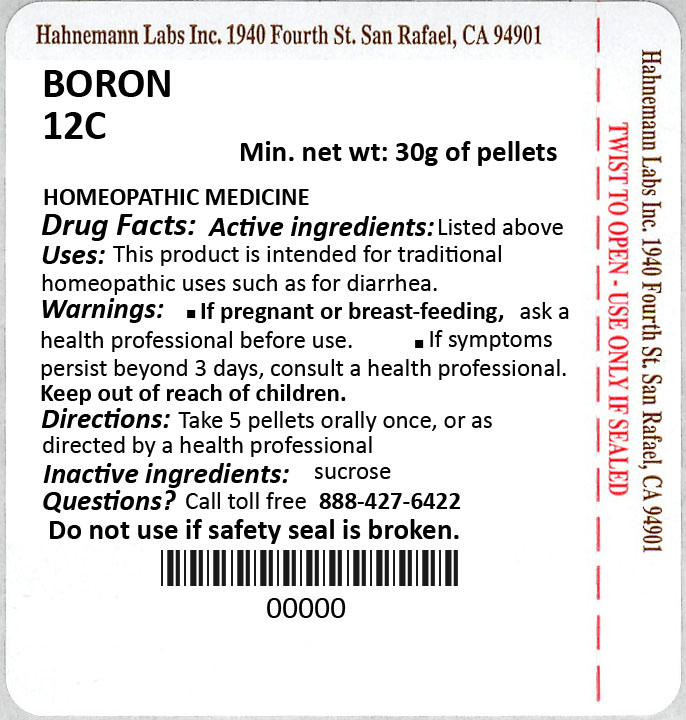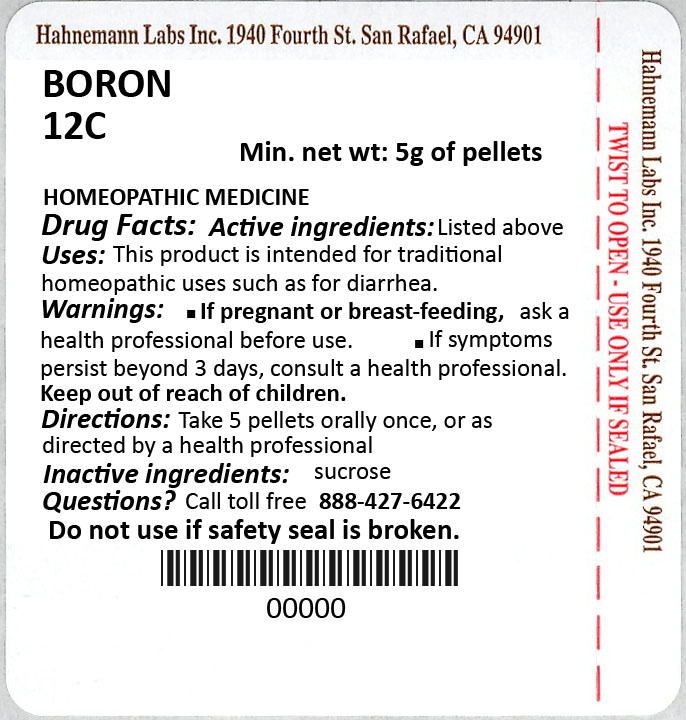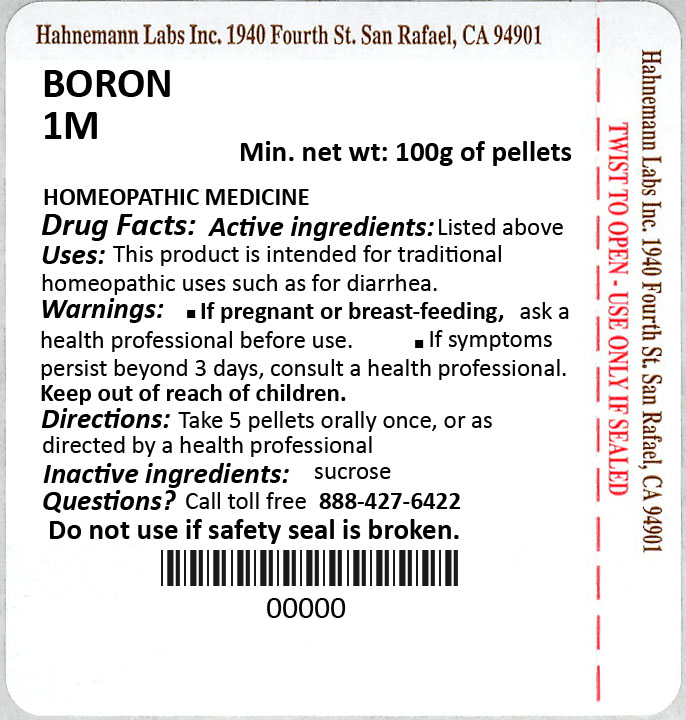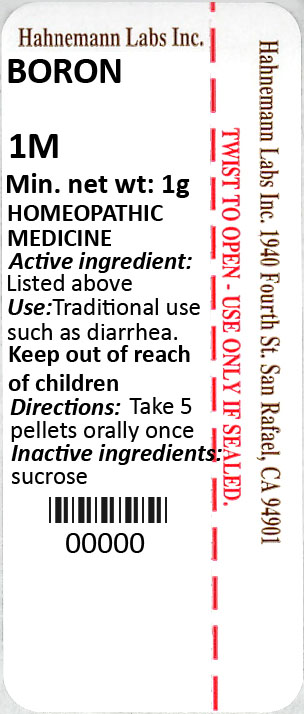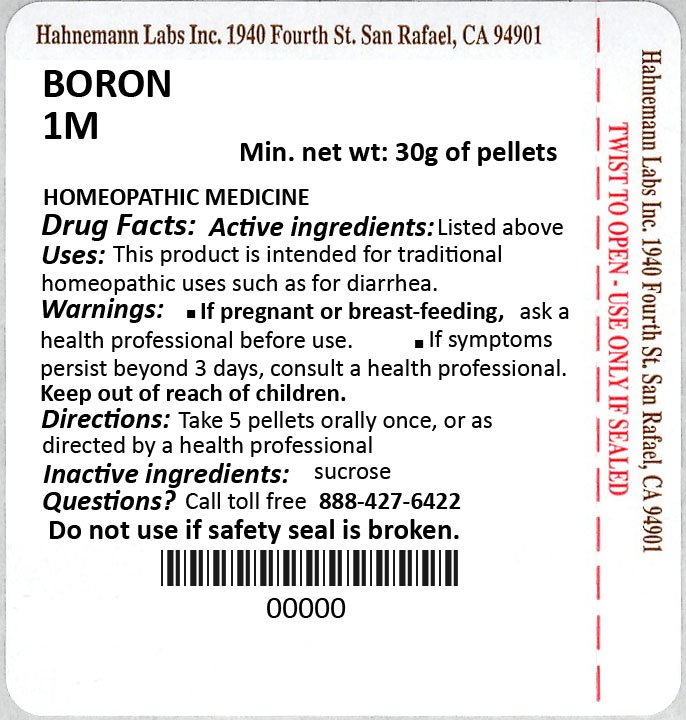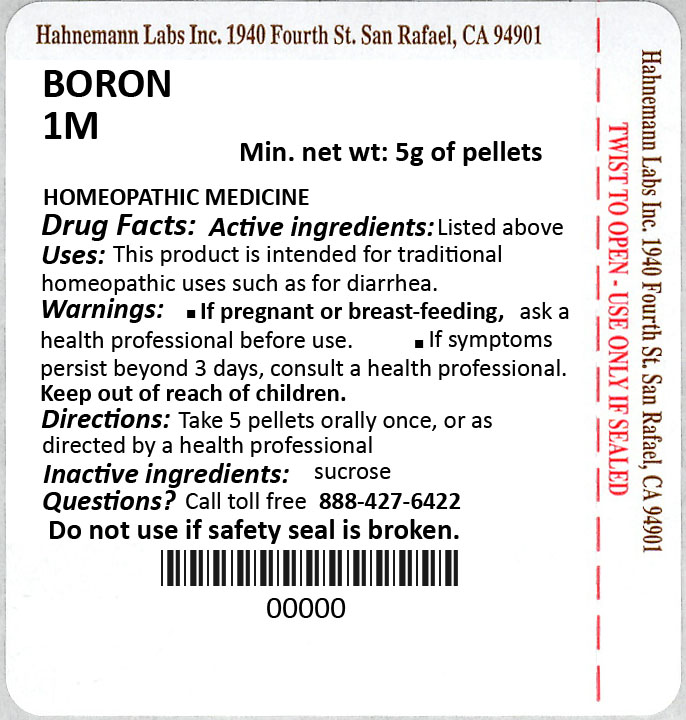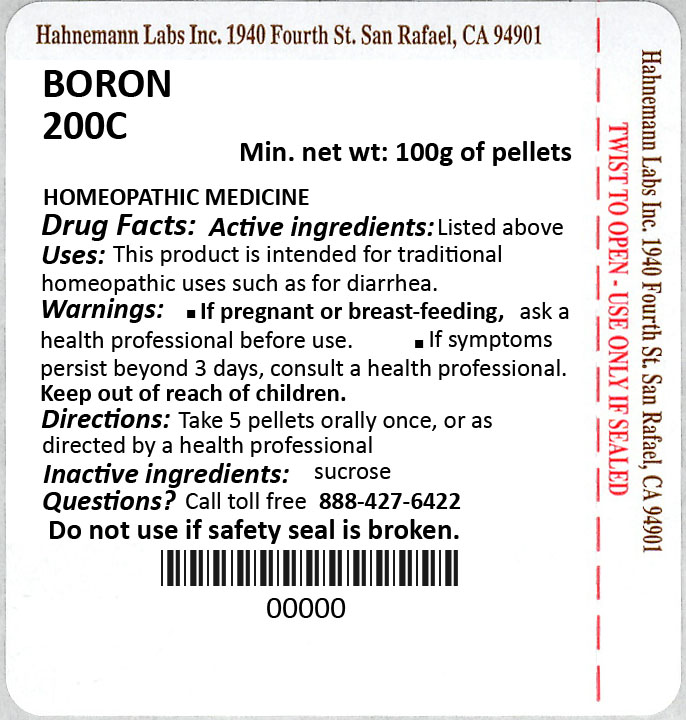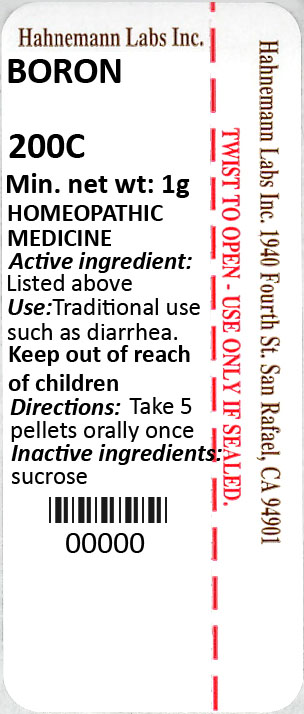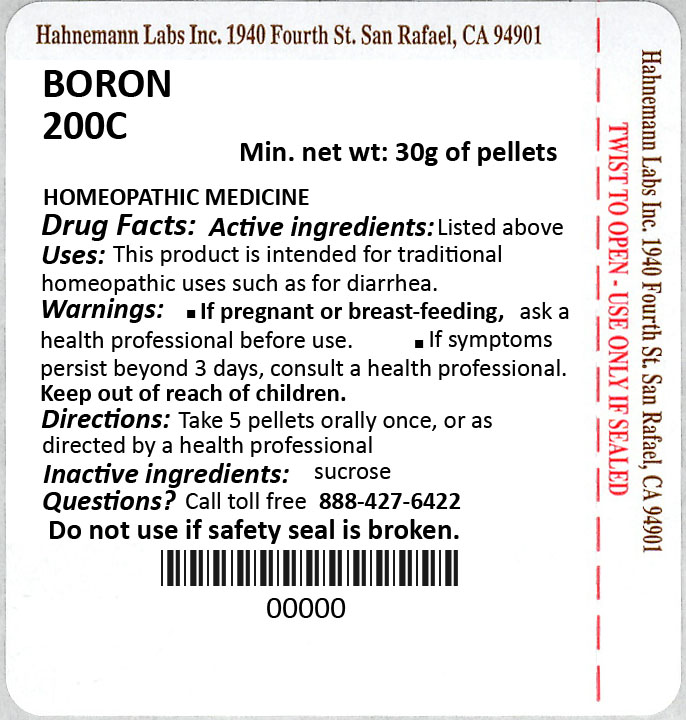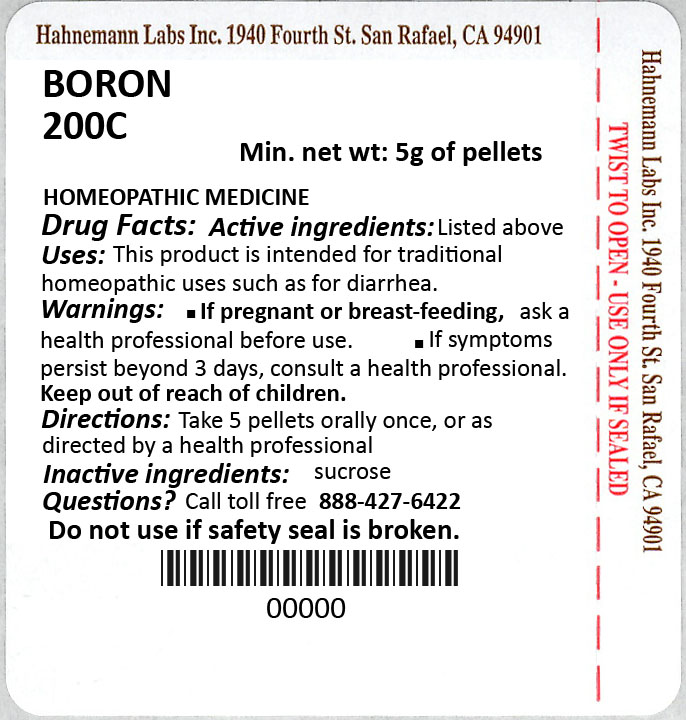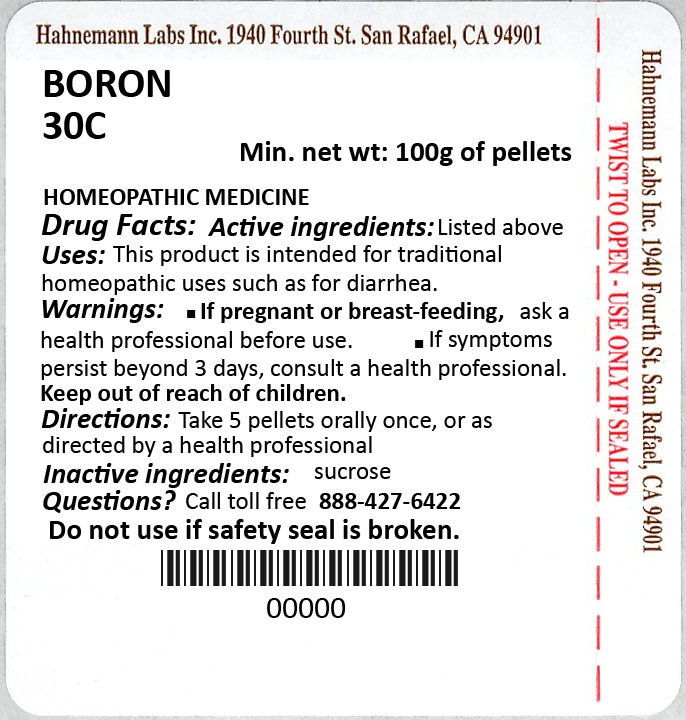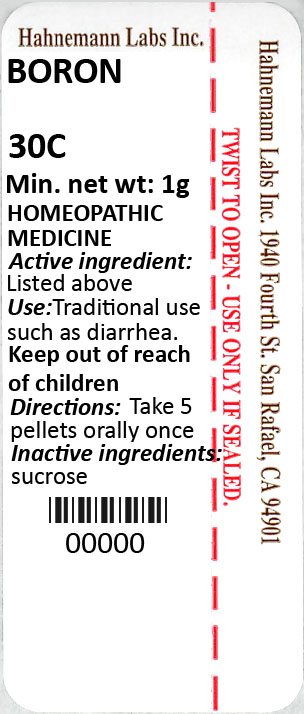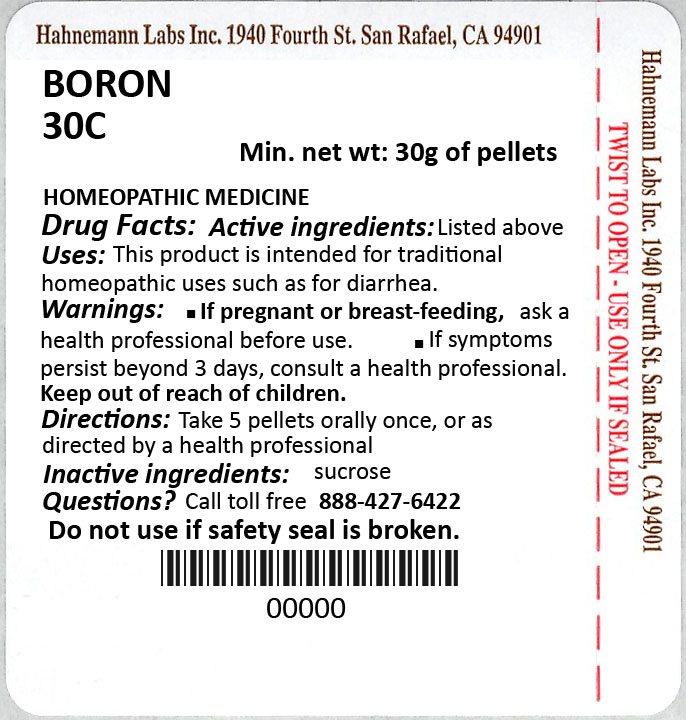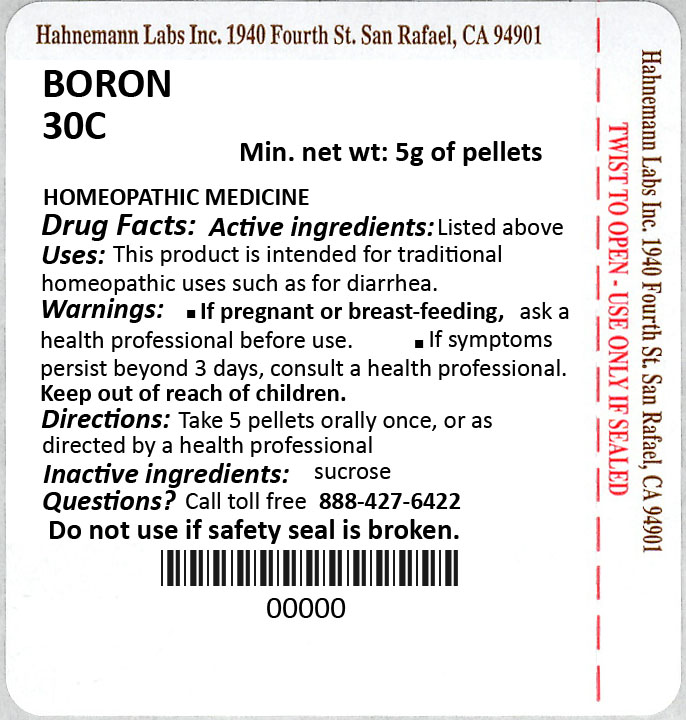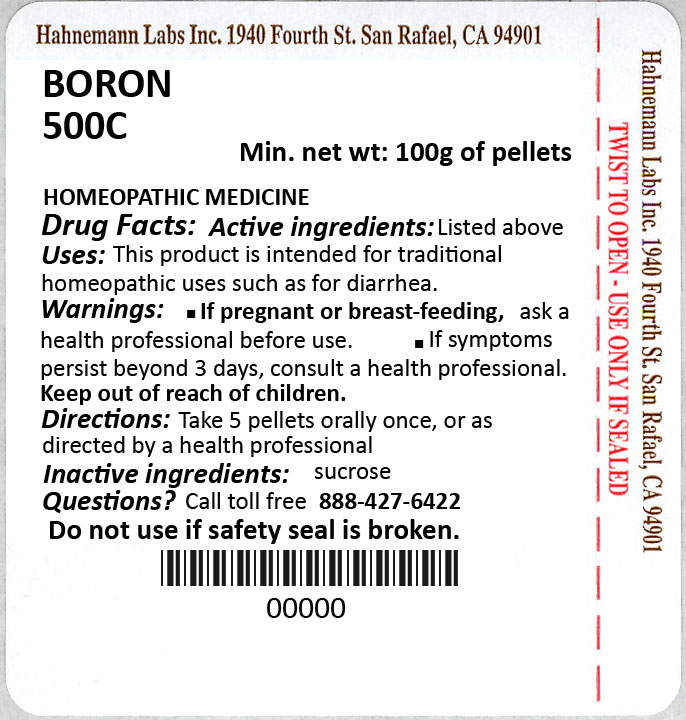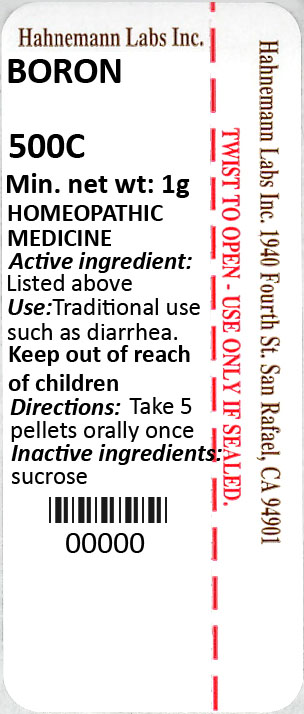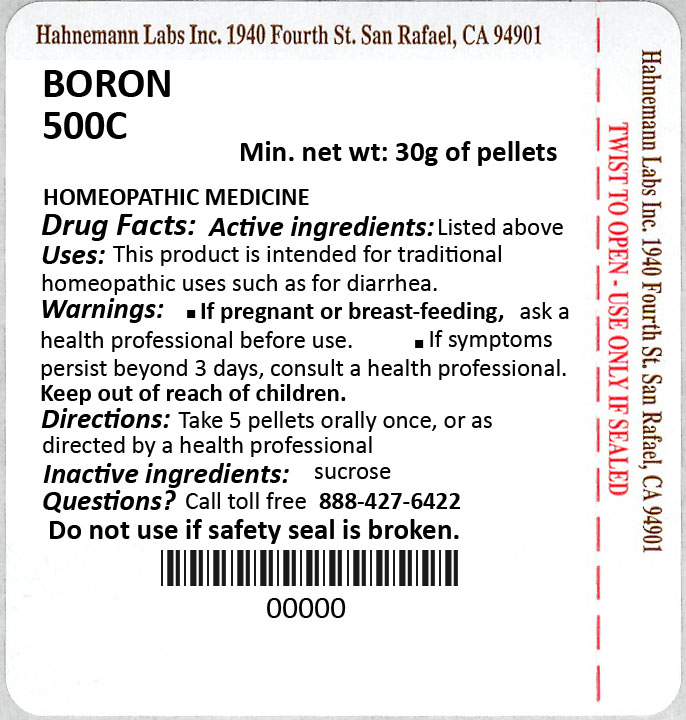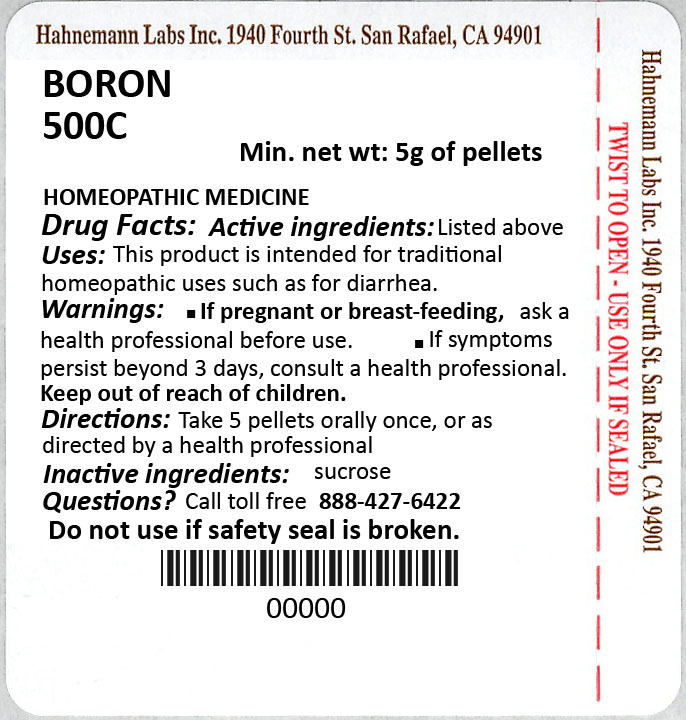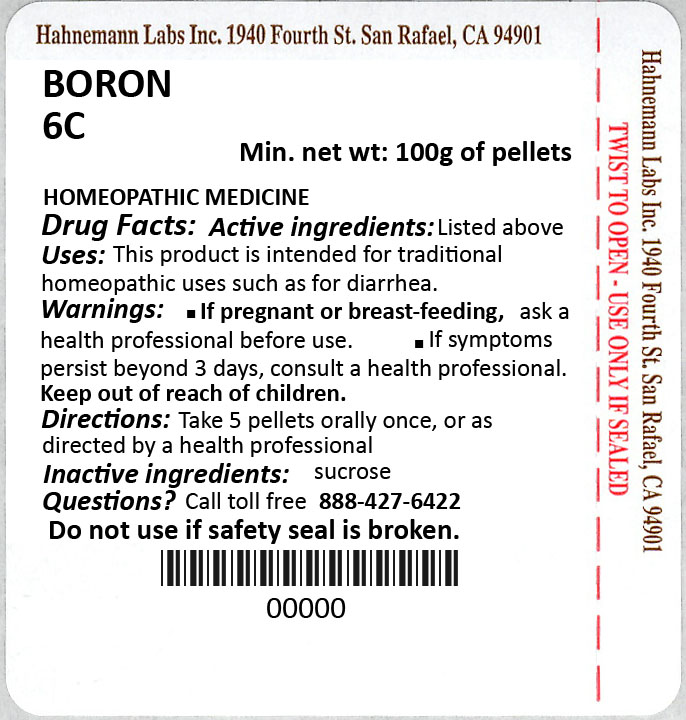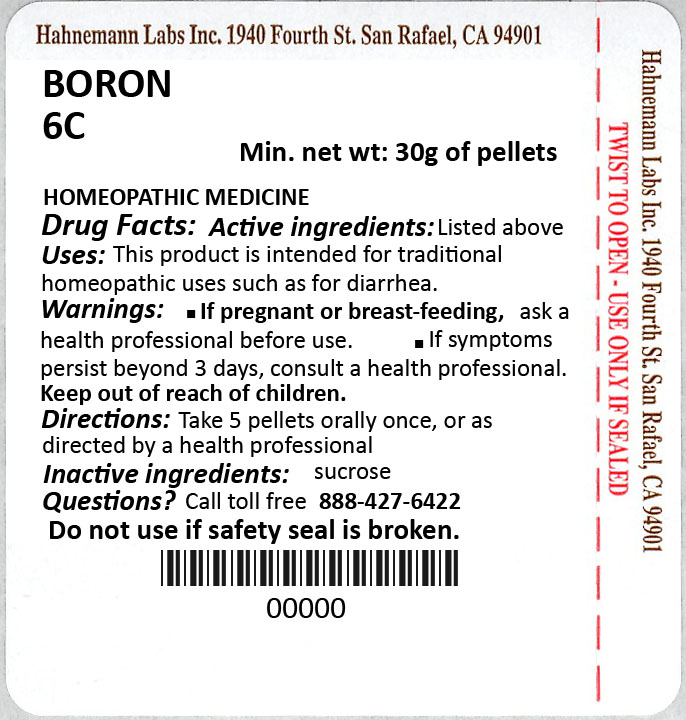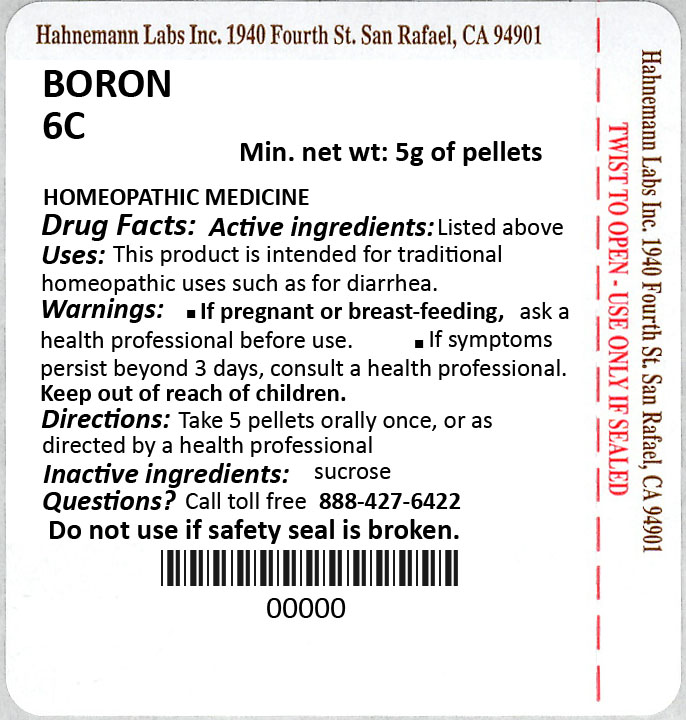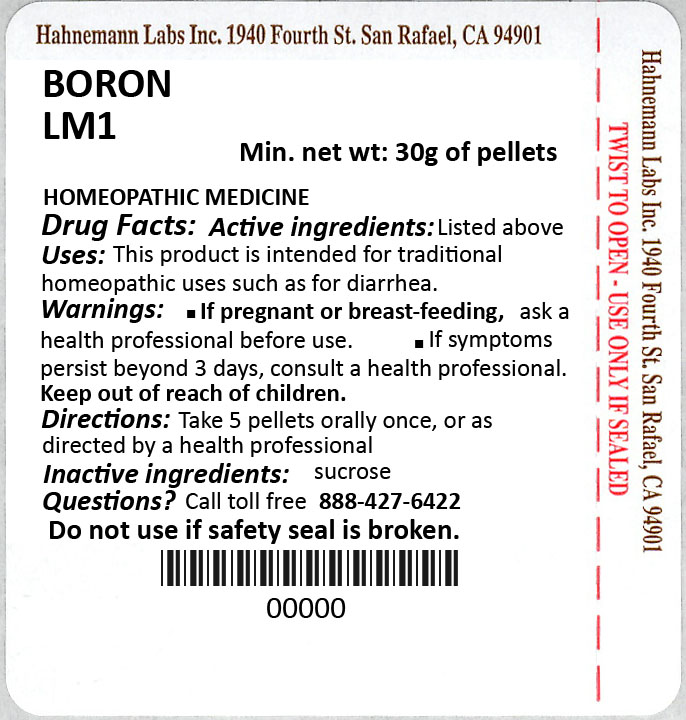 DRUG LABEL: Boron
NDC: 75929-109 | Form: PELLET
Manufacturer: Pharma Packaging Solutions, LLC dba Tjoapack LLC
Category: homeopathic | Type: HUMAN OTC DRUG LABEL
Date: 20260219

ACTIVE INGREDIENTS: BORON 30 [hp_C]/1 1
INACTIVE INGREDIENTS: SUCROSE

Boron (SinEcch-i)
(Packaged by Pharma Packaging Solutions, LLC dba Tjoapack LLC)